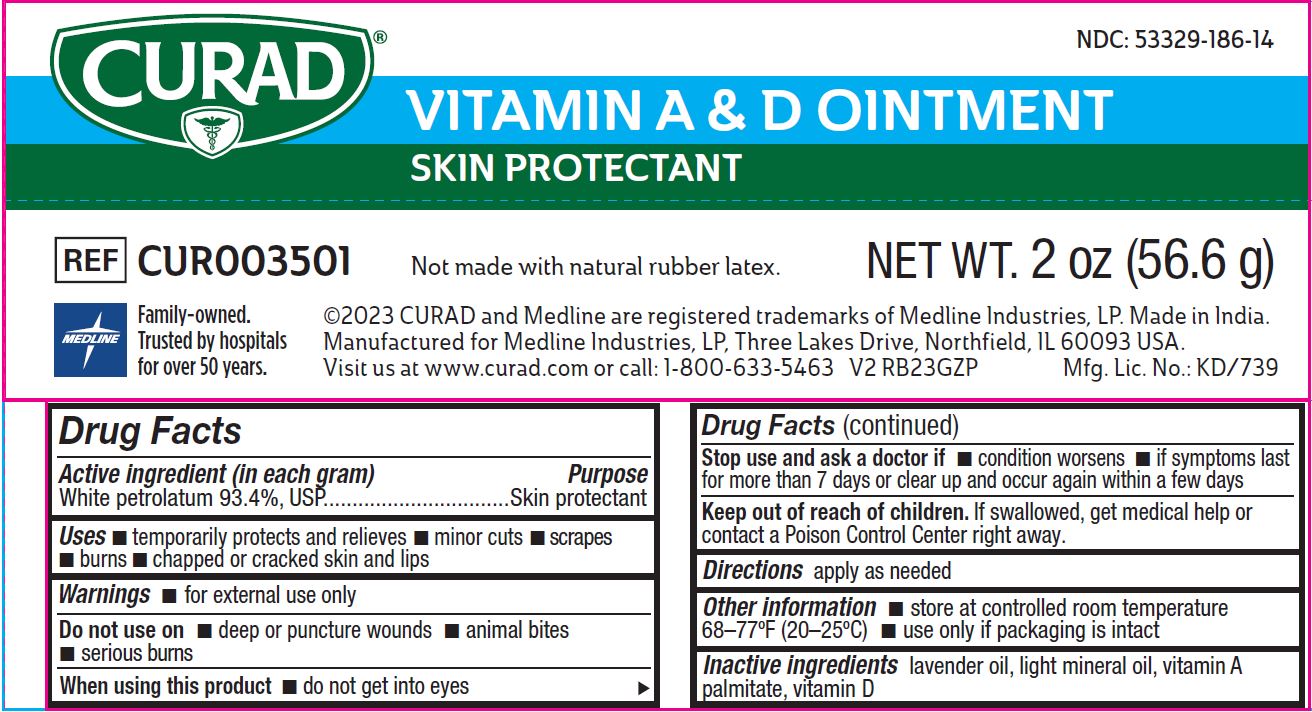 DRUG LABEL: Medline
NDC: 53329-186 | Form: OINTMENT
Manufacturer: Medline Industries, LP
Category: otc | Type: HUMAN OTC DRUG LABEL
Date: 20251104

ACTIVE INGREDIENTS: WHITE PETROLATUM 934 mg/1 g
INACTIVE INGREDIENTS: LIGHT MINERAL OIL; VITAMIN A PALMITATE; VITAMIN D; LAVENDER OIL

186 Curad Vitamin A&D ointment

Active ingredient (in each gram)

White petrolatum 93.4%, USP

Purpose

Skin protectant

Uses

- temporarily protects and relieves
- minor cuts
- scrapes
- burns
- chapped or cracked skin and lips

Warnings

for external use only

Do not use on

- deep or puncture wounds
- animal bites
- serious burns

When using this product

- do not get into eyes

Stop use and ask a doctor if

- condition worsens
- if symptoms last for more than 7 days or clear up and occur again within a few days

Keep out of reach of children.

If swallowed, get medical help or contact a Poison Control Center right away.

Directions

- apply as needed

Other information

- store at controlled room temperature 68-77°F (20-25°C)
- use only if packaging is intact

Inactive ingredients

lavender oil, light mineral oil, vitamin A palmitate, vitamin D

Manufacturing Information

©2023 CURAD and Medline are registered trademarks of Medline Industries, LP.

Made in India

Manufactured for Medline Industries, LP

Three Lakes Drive, Northfield, IL 60093 USA

Visit us at www.curad.com or call: 1-800-633-5463

REF: CUR003501